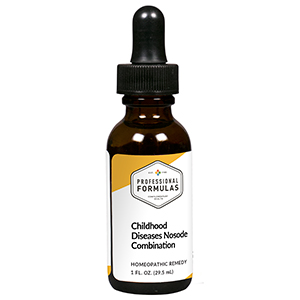 DRUG LABEL: Childhood Diseases Nosode Combination
NDC: 63083-9408 | Form: LIQUID
Manufacturer: Professional Complementary Health Formulas
Category: homeopathic | Type: HUMAN OTC DRUG LABEL
Date: 20190815

ACTIVE INGREDIENTS: AMARYLLIS BELLADONNA WHOLE 3 [hp_X]/29.5 mL; ARTEMISIA ANNUA FLOWERING TOP 3 [hp_X]/29.5 mL; GELSEMIUM SEMPERVIRENS ROOT 3 [hp_X]/29.5 mL; SOLANUM DULCAMARA WHOLE 4 [hp_X]/29.5 mL; PULSATILLA MONTANA WHOLE 4 [hp_X]/29.5 mL; OYSTER SHELL CALCIUM CARBONATE, CRUDE 8 [hp_X]/29.5 mL; MEASLES VIRUS 12 [hp_X]/29.5 mL; HISTATIN 3 12 [hp_X]/29.5 mL; DRABA VERNA WHOLE 12 [hp_X]/29.5 mL; HUMAN VARICELLA-ZOSTER IMMUNE GLOBULIN 12 [hp_X]/29.5 mL
INACTIVE INGREDIENTS: ALCOHOL; WATER

R408

ACTIVE INGREDIENTS

Belladonna 3X
Chamomilla 3X
Gelsemium sempervirens 3X
Dulcamara 4X
Pulsatilla 4X
Calcarea carbonica 8X
Morbillinum 12X
Parotitis 12X
Rubella 12X
Varicella 12X

QUESTIONS

Professional Formulas

PO Box 2034 Lake Oswego, OR 97035

INDICATIONS

For the temporary relief of occasional headache, fatigue, cough, runny nose, or minor sore throat.*

PURPOSE

*Claims based on traditional homeopathic practice, not accepted medical evidence. Not FDA evaluated.

WARNINGS

Persistent symptoms may be a sign of a serious condition. If symptoms persist or are accompanied by a fever, rash, or persistent headache, consult a doctor. Keep out of the reach of children. In case of overdose, get medical help or contact a poison control center right away. If pregnant or breastfeeding, ask a healthcare professional before use.

Keep out of the reach of children.

PREGNANCY OR BREAST FEEDING

If pregnant or breastfeeding, ask a healthcare professional before use.

DIRECTIONS

Place drops under tongue 30 minutes before/after meals. Adults and children 12 years and over: Take 10 to 15 drops once weekly or monthly. If mild symptoms are present, take 10 drops up to 3 times per day. Consult a physician for use in children under 12 years of age.

OTHER INFORMATION

Tamper resistant. If seal is broken, do not use. After opening, close container tightly and store at room temperature away from heat.

INACTIVE INGREDIENTS

40% ethanol, purified water.

LABEL

Est 1985

Professional Formulas

Complementary Health

Childhood Diseases Nosode Combination

Homeopathic Remedy

1 FL. OZ. (29.5 mL)